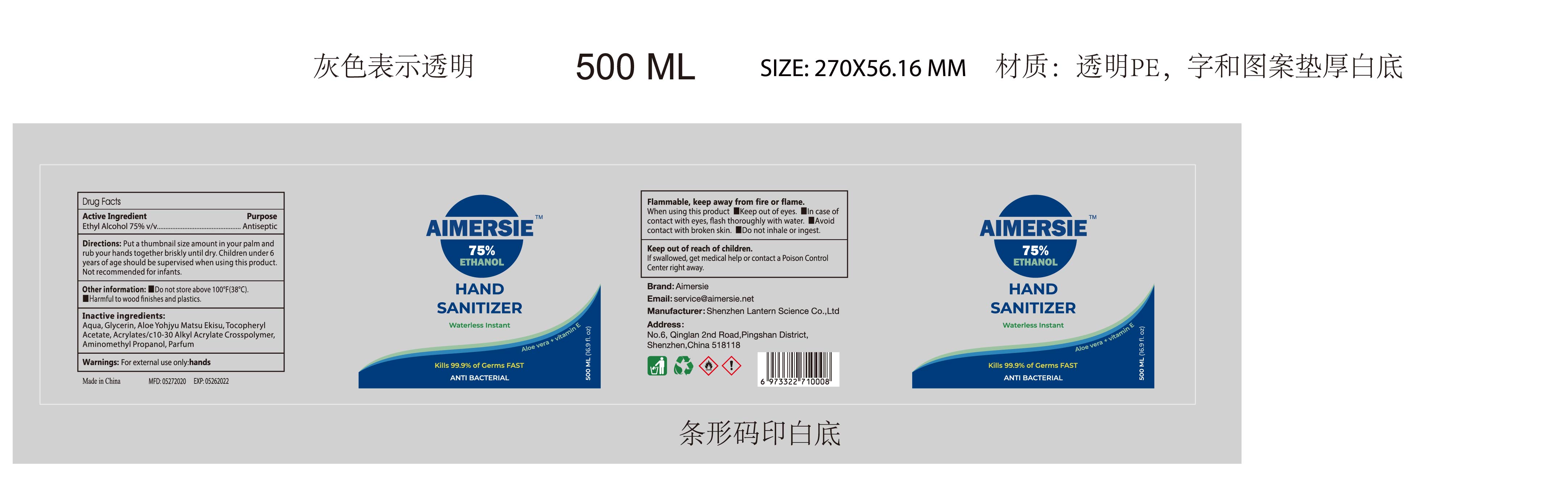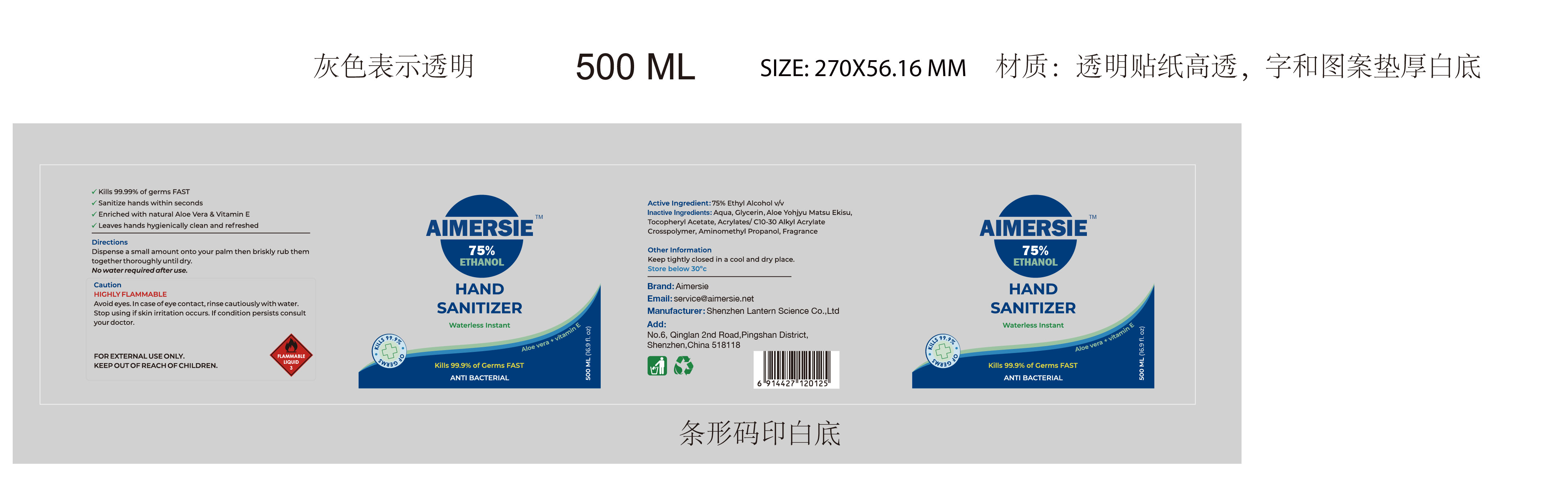 DRUG LABEL: AIMERSIE hand santizer 500ml
NDC: 54860-232 | Form: LIQUID
Manufacturer: Shenzhen Lantern Science Co.,Ltd
Category: otc | Type: HUMAN OTC DRUG LABEL
Date: 20210227

ACTIVE INGREDIENTS: ALCOHOL 75 mL/100 mL
INACTIVE INGREDIENTS: ALOE 0.15 mL/100 mL; WATER 23.85 mL/100 mL; AMINOMETHYLPROPANOL 0.09 mL/100 mL; CARBOMER INTERPOLYMER TYPE A (55000 CPS) 0.000008 mL/100 mL; GLYCERIN 0.5 mL/100 mL; ALOE ANDONGENSIS WHOLE 0.1 mL/100 mL; .ALPHA.-TOCOPHEROL ACETATE 0.01 mL/100 mL

AIMERSIE hand santizer 500ml

Active Ingredient

Active Ingredients Purpose

Ethyl Alcoh75% Antiseptic

purpose

ANTI BACTERIAL

DOSAGE AND ADMINISTRATION

Recommended for repeated use.

use anywhere without water.

Caution

HIGHLY FLAMMABLE

Avoid eyes.In case of eye contact,rinse cautiously with water.

Stop using if skin irritation ocurs.If condition persists consult your doctor.

For external use only.

WARNINGS AND PRECAUTIONS

For external use only.

Flammable, keep away from heat and flame.

STOP USE

Discontinue if skin becomes irritated and ask a doctor .

Keep out of reach of children. In case of accidental ingestion, seek professional assistance or contact a poson control center immediately.

Inactive ingredient

Aqua，Glycerin，Aloe Yohjyu Matsu Ekisu，Tocopheryl Acetate，Acrylates/C10-30 Alkyl Acrylate Crosspolymer，Aminomethyl Propanol，Fragrance

Directions

Dispense a small amount onto your palm then briskly rub them together thoroughly until dry.

No water required after use

When using this product

keep out of eyes. In case of contact with eyes, flush thoroughly with water.

Do not inhale or ingest.

Avoid contact with broken skin.

Other information

Do not store above 105F.

May discolor some fabrics.

Harmful to wood finishes and plastics.

Feature

Kills 99.99% of germs Fast

Sanitize hands within seconds

Enriched with natural Aloe Vera&Vitamin E

Laeves hands hygienically clean and refreshed.

Other information

Keep tightly closed in a cool and dry place.

Store below 30℃